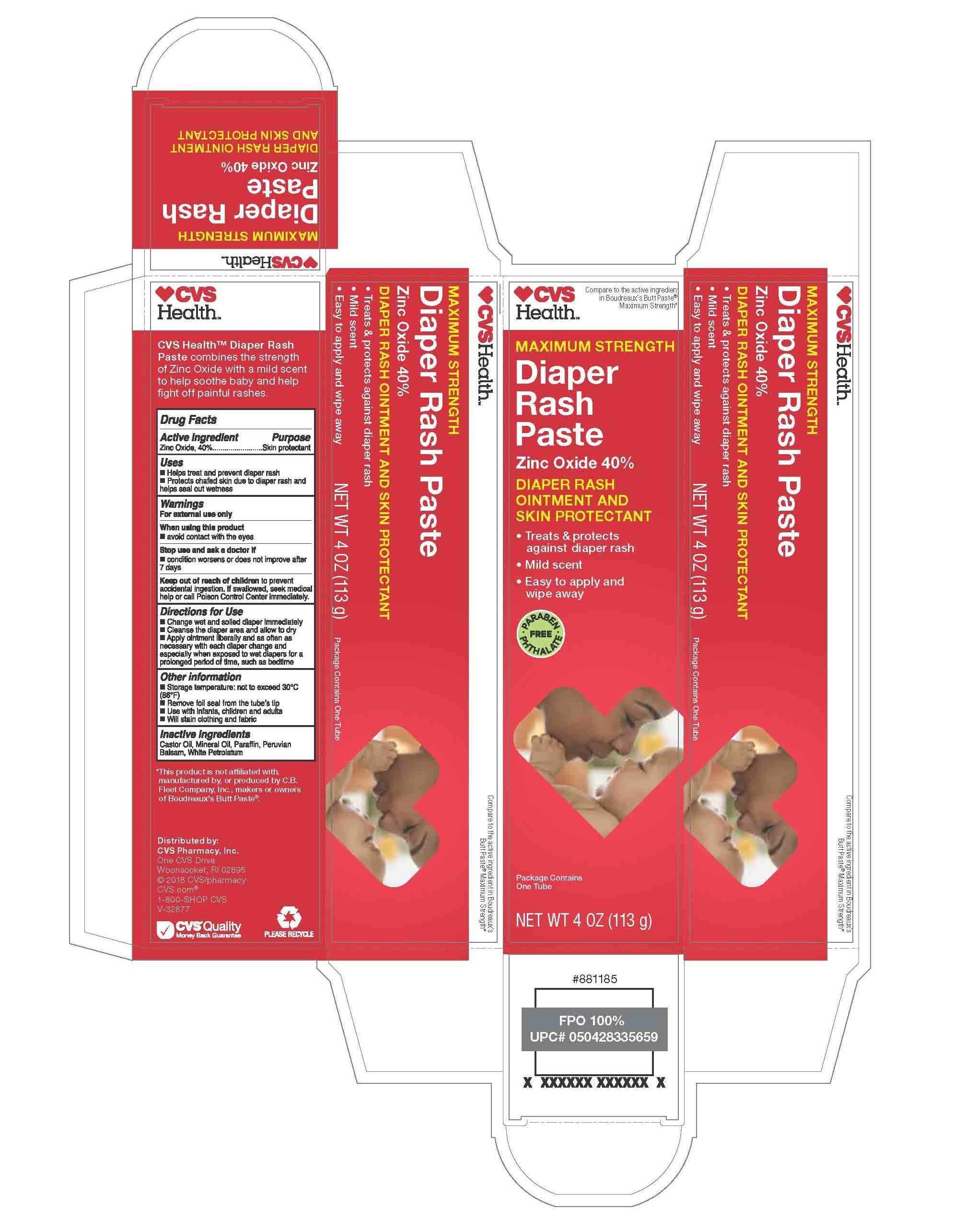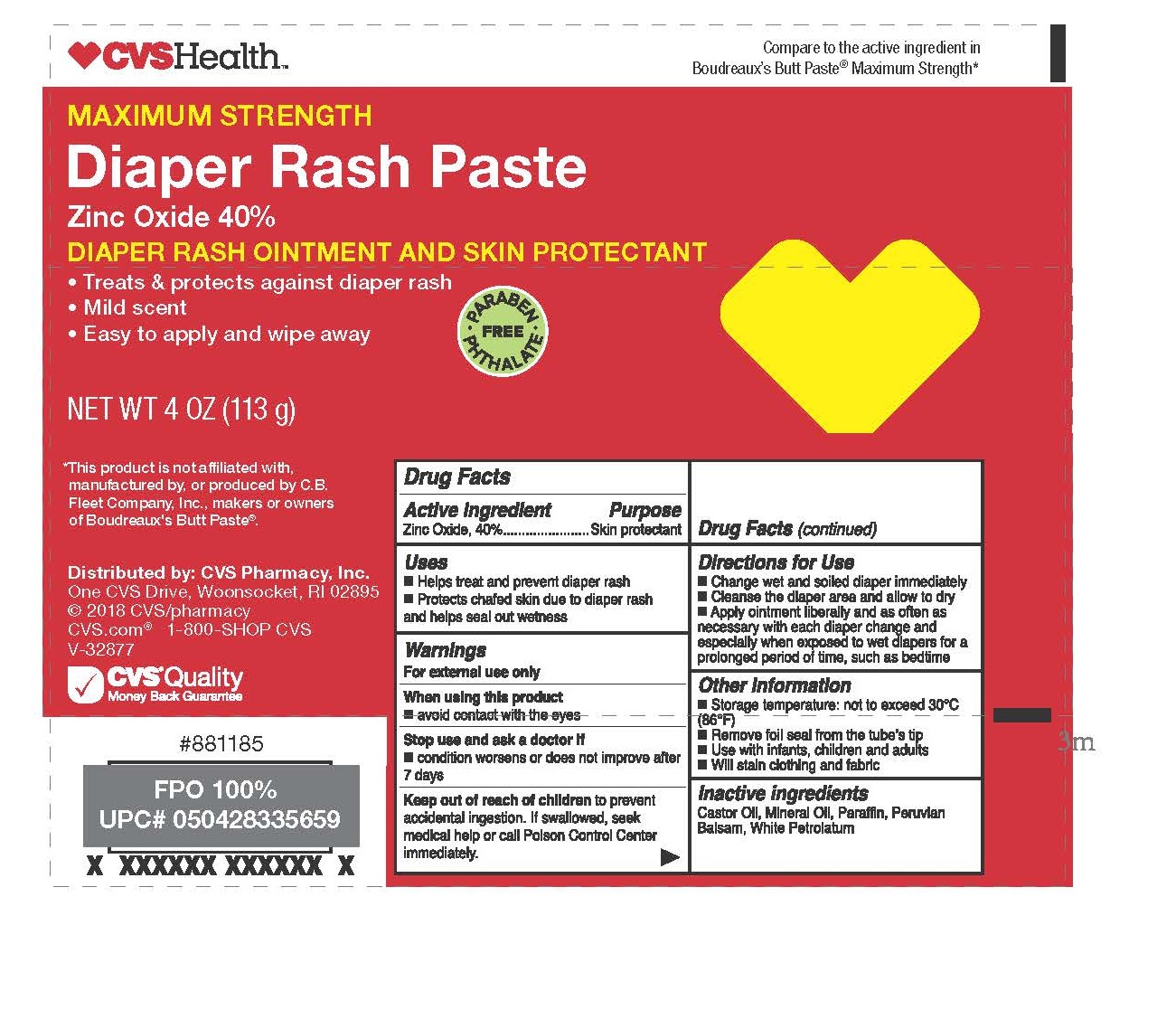 DRUG LABEL: Maximum Strength Diaper Rash
NDC: 59779-849 | Form: OINTMENT
Manufacturer: CVS Pharmacy
Category: otc | Type: HUMAN OTC DRUG LABEL
Date: 20210129

ACTIVE INGREDIENTS: ZINC OXIDE 40 g/100 g
INACTIVE INGREDIENTS: PETROLATUM 31 g/100 g; MINERAL OIL 20 g/100 g; PARAFFIN 1 g/100 g; CASTOR OIL 3.5 g/100 g; BALSAM PERU 4.5 g/100 g

Active ingredient

Zinc Oxide, 40%

Purpose

Skin protectant

Uses

helps treat and prevent diaper rash, Protects chafed skin due to diaper rash and helps seal out wetness

Warnings

For external use only.

When using this product

avoid contact with the eyes

Stop use and ask a doctor if

condition worsens or does not improve after 7 days

Keep out of reach of children

to prevent accidential ingestion. If swallowed, seek medical help or call Poison Control Center immediately.

Directions for Use

change wet and soiled diaper immediately, cleanse the diaper area and allow to dry, apply ointment liberally as often as necessary with each diaper change and especially when exposured to wet diapers for a prolonged period of time, such as bedtime

Other information

Storage temperature: not to exceed 30oC (86oF),

Remove foil seal from the tube's tip,

Use with infants, children, and adults,

Will stain clothing and fabric

Inactive ingredients

Castor Oil, Mineral Oil, Paraffin, Peruvian Balsam, White Petrolatum